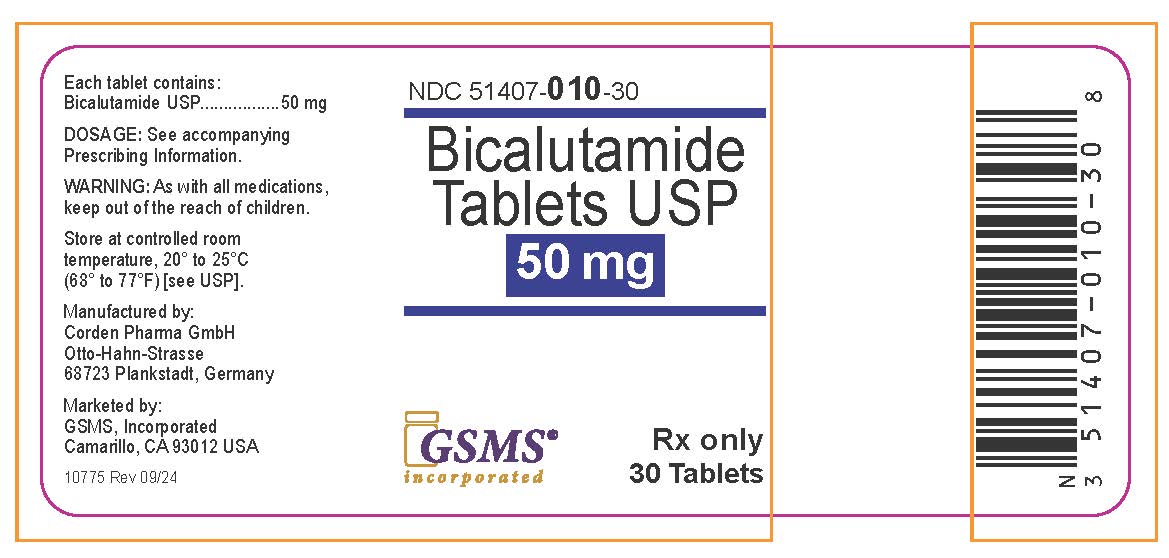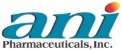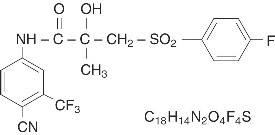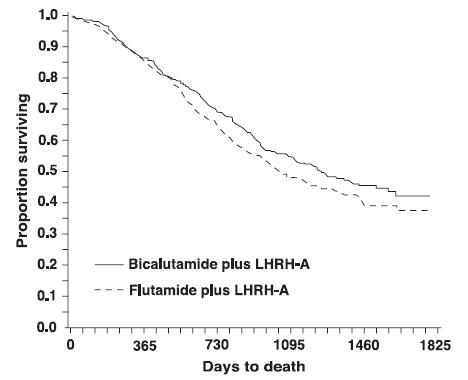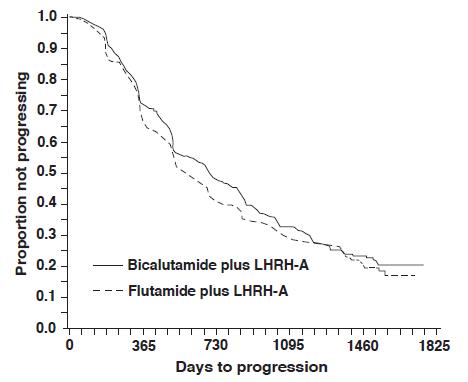 DRUG LABEL: Bicalutamide
NDC: 51407-010 | Form: TABLET
Manufacturer: Golden State Medical Supply, Inc.
Category: prescription | Type: HUMAN PRESCRIPTION DRUG LABEL
Date: 20251210

ACTIVE INGREDIENTS: BICALUTAMIDE 50 mg/1 1
INACTIVE INGREDIENTS: LACTOSE MONOHYDRATE; HYPROMELLOSE, UNSPECIFIED; POLYETHYLENE GLYCOL 300; SODIUM STARCH GLYCOLATE TYPE A POTATO; POVIDONE K30; TITANIUM DIOXIDE; MAGNESIUM STEARATE

HIGHLIGHTS OF PRESCRIBING INFORMATION

BICALUTAMIDE TABLETS. These highlights do not include all the information needed to use BICALUTAMIDE TABLETS safely and effectively. See full prescribing information for BICALUTAMIDE TABLETS.
BICALUTAMIDE tablets, for oral use
Initial U.S. Approval: 1995

1. INDICATIONS AND USAGE

- Bicalutamide tablets 50 mg is an androgen receptor inhibitor indicated for use in combination therapy with a luteinizing hormone-releasing hormone (LHRH) analog for the treatment of Stage D2metastatic carcinoma of the prostate. (1)
- Bicalutamide tablets 150 mg daily is not approved for use alone or with other treatments. (1)

2. DOSAGE AND ADMINISTRATION

The recommended dose for bicalutamide therapy in combination with an LHRH analog is one 50 mg tablet once daily (morning or evening). (2)

3. DOSAGE FORMS AND STRENGTHS

50 mg tablets (3)

4. CONTRAINDICATIONS

- Hypersensitivity (4)
- Women (4)
- Pregnancy (4, 8.1)

5. WARNINGS AND PRECAUTIONS

- Severe hepatic injury and fatal hepatic failure have been observed. Monitor serum transaminase levels prior to starting treatment with bicalutamide, at regular intervals for the first four months of treatment and periodically thereafter, and for symptoms or signs suggestive of hepatic dysfunction. Use bicalutamide with caution in patients with hepatic impairment. (5.1)
- Hemorrhage with Concomitant Use of Coumarin Anticoagulant. Closely monitor the Prothrombin Time (PT) and International Normalized Ratio (INR), and adjust the anticoagulant dose as needed. (5.2)
- Gynecomastia and breast pain have been reported during treatment with bicalutamide 150 mg when used as a single agent. (5.3)
- Bicalutamide is used in combination with an LHRH agonist. LHRH agonists have been shown to cause a reduction in glucose tolerance in males. Consideration should be given to monitoring blood glucose in patients receiving bicalutamide in combination with LHRH agonists. (5.4)
- Monitoring Prostate Specific Antigen (PSA) is recommended. Evaluate for clinical progression if PSA increases. (5.5)

6. ADVERSE REACTIONS

Adverse reactions that occurred in more than 10% of patients receiving bicalutamide plus an LHRH-A were: hot flashes, pain (including general, back, pelvic and abdominal), asthenia, constipation, infection, nausea, peripheral edema, dyspnea, diarrhea, hematuria, nocturia, and anemia. (6.1)

To report SUSPECTED ADVERSE REACTIONS, contact ANI Pharmaceuticals, Inc. at 1-800-308-6755 or FDA at 1-800-FDA-1088 or www.fda.gov/medwatch

7. DRUG INTERACTIONS

- R-bicalutamide is an inhibitor of CYP 3A4; therefore, caution should be used when bicalutamide is co-administered with CYP 3A4 substrates. (7)
- PT/INR should be closely monitored in patients already receiving coumarin anticoagulants who are started on bicalutamide. (7)

8. USE IN SPECIFIC POPULATIONS

- Females and Males of Reproductive Potential: Advise males with female partners of reproductive potential to use effective contraception. (8.3)
- Pediatric patients: Efficacy has not been demonstrated for the treatment of familial male-limited precocious puberty (testotoxicosis). (8.4)

FULL PRESCRIBING INFORMATION

1. INDICATIONS AND USAGE

Bicalutamide tablets 50 mg daily is indicatedfor use in combination therapy with a luteinizing hormone-releasing hormone (LHRH) analog for the treatment of Stage D2metastatic carcinoma of the prostate.

Bicalutamide tablets 150 mg daily is not approvedfor use alone or with other treatments [see Clinical Studies (14.2)].

2. DOSAGE AND ADMINISTRATION

2.1. Recommended Dose and Schedule

The recommended dose for bicalutamide therapy in combination with an LHRH analog is one 50 mg tablet once daily (morning or evening), with or without food. It is recommended that bicalutamide tablets be taken at the same time each day. Treatment with bicalutamide tablets should be started at the same time as treatment with an LHRH analog. If a dose of bicalutamide tablets is missed, take the next dose at the scheduled time. Do not take the missed dose and do not double the next dose.

2.2. Dosage Adjustment in Renal Impairment

No dosage adjustment is necessary for patients with renal impairment [see Use in Specific Populations (8.7)] .

2.3. Dosage Adjustment in Hepatic Impairment

No dosage adjustment is necessary for patients with mild to moderate hepatic impairment. In patients with severe liver impairment (n=4), although there was a 76% increase in the half-life (5.9 and 10.4 days for normal and impaired patients, respectively) of the active enantiomer of bicalutamide no dosage adjustment is necessary [see Use in Specific Populations (8.6)] .

3. DOSAGE FORMS AND STRENGTHS

Bicalutamide Tablets USP 50 mg for oral administration.

4. CONTRAINDICATIONS

Bicalutamide tablets are contraindicated in:

- Hypersensitivity

Bicalutamide tablets are contraindicated in any patient who has shown a hypersensitivity reaction to the drug or any of the tablet’s components. Hypersensitivity reactions including angioneurotic edema and urticaria have been reported.

- Women

Bicalutamide tablets have no indication for women, and should not be used in this population.

- Pregnancy

Bicalutamide tablets can cause fetal harm when administered to a pregnant woman [see Use in Specific Populations (8.1)] .

5. WARNINGS AND PRECAUTIONS

5.1. Hepatitis

Cases of death or hospitalization due to severe liver injury (hepatic failure) have been reported postmarketing in association with the use of bicalutamide tablets. Hepatotoxicity in these reports generally occurred within the first three to four months of treatment. Hepatitis or marked increases in liver enzymes leading to drug discontinuation occurred in approximately 1% of bicalutamide tablet patients in controlled clinical trials.

Serum transaminase levels should be measured prior to starting treatment with bicalutamide tablets, at regular intervals for the first four months of treatment, and periodically thereafter. If clinical symptoms or signs suggestive of liver dysfunction occur (e.g., nausea, vomiting, abdominal pain, fatigue, anorexia, “flu-like” symptoms, dark urine, jaundice, or right upper quadrant tenderness), the serum transaminases, in particular the serum ALT, should be measured immediately. If at any time a patient has jaundice, or their ALT rises above two times the upper limit of normal, bicalutamide tablets should be immediately discontinued with close follow-up of liver function.

5.2. Hemorrhage with Concomitant Use of Coumarin Anticoagulant

In the postmarketing setting, there have been reports of excessive prolongation of the prothrombin time (PT) and International Normalized Ratio (INR) days to weeks after the introduction of bicalutamide in patients who were previously stable on coumarin anticoagulants. Some patients had serious bleeding including intracranial, retroperitoneal, and gastrointestinal requiring blood transfusion and/or administration of vitamin K. Closely monitor the PT/INR, and adjust the anticoagulant dose as needed [see Drug Interactions (7)and Adverse Reactions (6.2)].

5.3. Gynecomastia and Breast Pain

In clinical trials with bicalutamide 150 mg as a single agent for prostate cancer, gynecomastia and breast pain have been reported in up to 38% and 39% of patients, respectively.

5.4. Glucose Tolerance

A reduction in glucose tolerance has been observed in males receiving LHRH agonists. This may manifest as diabetes or loss of glycemic control in those with pre-existing diabetes. Consideration should therefore be given to monitoring blood glucose in patients receiving bicalutamide in combination with LHRH agonists.

5.5. Laboratory Tests

Regular assessments of serum Prostate Specific Antigen (PSA) may be helpful in monitoring the patient’s response. If PSA levels rise during bicalutamide therapy, the patient should be evaluated for clinical progression. For patients who have objective progression of disease together with an elevated PSA, a treatment-free period of antiandrogen, while continuing the LHRH analog, may be considered.

6. ADVERSE REACTIONS

Because clinical trials are conducted under widely varying conditions, adverse reaction rates observed in the clinical trials of a drug cannot be directly compared to rates in the clinical trials of another drug and may not reflect the rates observed in practice.

6.1. Clinical Trials Experience

In patients with advanced prostate cancer treated with bicalutamide in combination with an LHRH analog, the most frequent adverse reaction was hot flashes (53%).

In the multi-center, double-blind, controlled clinical trial comparing bicalutamide 50 mg once daily with flutamide 250 mg three times a day, each in combination with an LHRH analog, the following adverse reactions with an incidence of 5% or greater, regardless of causality, have been reported.

Table 1. Incidence of Adverse Reactions (≥ 5% in Either Treatment Group) Regardless of Causality
Body System Adverse Reaction | Treatment Group Number of Patients (%)
 | Bicalutamide Plus LHRH Analog (n=401) | Flutamide Plus LHRH Analog (n=407)
Body as a Whole
Pain (General) | 142 (35) | 127 (31)
Back Pain | 102 (25) | 105 (26)
Asthenia | 89 (22) | 87 (21)
Pelvic Pain | 85 (21) | 70 (17)
Infection | 71 (18) | 57 (14)
Abdominal Pain | 46 (11) | 46 (11)
Chest Pain | 34 (8) | 34 (8)
Headache | 29 (7) | 27 (7)
Flu Syndrome | 28 (7) | 30 (7)
Cardiovascular
Hot Flashes | 211 (53) | 217 (53)
Hypertension | 34 (8) | 29 (7)
Digestive
Constipation | 87 (22) | 69 (17)
Nausea | 62 (15) | 58 (14)
Diarrhea | 49 (12) | 107 (26)
Increased Liver Enzyme Test | 30 (7) | 46 (11)
Dyspepsia | 30 (7) | 23 (6)
Flatulence | 26 (6) | 22 (5)
Anorexia | 25 (6) | 29 (7)
Vomiting | 24 (6) | 32 (8)
Hemic and Lymphatic
Anemia | 45 (11) | 53 (13)
Metabolic and Nutritional
Peripheral Edema | 53 (13) | 42 (10)
Weight Loss | 30 (7) | 39 (10)
Hyperglycemia | 26 (6) | 27 (7)
Alkaline Phosphatase Increased | 22 (5) | 24 (6)
Weight Gain | 22 (5) | 18 (4)
Musculoskeletal
Bone Pain | 37 (9) | 43 (11)
Myasthenia | 27 (7) | 19 (5)
Arthritis | 21 (5) | 29 (7)
Pathological Fracture | 17 (4) | 32 (8)
Nervous System
Dizziness | 41 (10) | 35 (9)
Paresthesia | 31 (8) | 40 (10)
Insomnia | 27 (7) | 39 (10)
Anxiety | 20 (5) | 9 (2)
Depression | 16 (4) | 33 (8)
Respiratory System
Dyspnea | 51 (13) | 32 (8)
Cough Increased | 33 (8) | 24 (6)
Pharyngitis | 32 (8) | 23 (6)
Bronchitis | 24 (6) | 22 (3)
Pneumonia | 18 (4) | 19 (5)
Rhinitis | 15 (4) | 22 (5)
Skin and Appendages
Rash | 35 (9) | 30 (7)
Sweating | 25 (6) | 20 (5)
Urogenital
Nocturia | 49 (12) | 55 (14)
Hematuria | 48 (12) | 26 (6)
Urinary Tract Infection | 35 (9) | 36 (9)
Gynecomastia | 36 (9) | 30 (7)
Impotence | 27 (7) | 35 (9)
Breast Pain | 23 (6) | 15 (4)
Urinary Frequency | 23 (6) | 29 (7)
Urinary Retention | 20 (5) | 14 (3)
Urinary Impaired | 19 (5) | 15 (4)
Urinary Incontinence | 15 (4) | 32 (8)

Other adverse reactions (greater than or equal to 2%, but less than 5%) reported in the bicalutamide-LHRH analog treatment group are listed below by body system and are in order of decreasing frequency within each body system regardless of causality.

Body as a Whole:Neoplasm; Neck Pain; Fever; Chills; Sepsis; Hernia; Cyst

Cardiovascular:Angina Pectoris; Congestive Heart Failure; Myocardial Infarct; Heart Arrest; Coronary Artery Disorder; Syncope

Digestive:Melena; Rectal Hemorrhage; Dry Mouth; Dysphagia; Gastrointestinal Disorder; Periodontal Abscess; Gastrointestinal Carcinoma

Metabolic and Nutritional:Edema; BUN Increased; Creatinine Increased; Dehydration; Gout; Hypercholesteremia

Musculoskeletal:Myalgia; Leg Cramps

Nervous:Hypertonia; Confusion; Somnolence; Libido Decreased; Neuropathy; Nervousness

Respiratory:Lung Disorder; Asthma; Epistaxis; Sinusitis

Skin and Appendages:Dry Skin; Alopecia; Pruritus; Herpes Zoster; Skin Carcinoma; Skin Disorder

Special Senses:Cataract Specified

Urogenital:Dysuria; Urinary Urgency; Hydronephrosis; Urinary Tract Disorder

Abnormal Laboratory Test Values:
Laboratory abnormalities including: elevated AST, ALT, bilirubin, BUN, and creatinine; and decreased hemoglobin and white cell count, have been reported in both bicalutamide-LHRH analog treated and flutamide-LHRH analog treated patients.

6.2. Postmarketing Experience

The following adverse reactions have been identified during post-approval use of bicalutamide. Because these reactions are reported voluntarily from a population of uncertain size, it is not always possible to reliably estimate their frequency or establish a causal relationship to drug exposure.

Respiratory disorders:Interstitial lung disease (some fatal) including interstitial pneumonitis and pulmonary fibrosis, most often at doses greater than 50 mg.

Hemorrhage:Increased PT/INR due to interaction between coumarin anticoagulants and bicalutamide. Serious bleeding reported. [see Warnings and Precautions (5.2)]

Skin and subcutaneous tissue disorders:Photosensitivity

7. DRUG INTERACTIONS

Clinical studies have not shown any drug interactions between bicalutamide and LHRH analogs (goserelin or leuprolide). There is no evidence that bicalutamide induces hepatic enzymes.

In vitrostudies have shown that R-bicalutamide is an inhibitor of CYP 3A4 with lesser inhibitory effects on CYP 2C9, 2C19 and 2D6 activity. Clinical studies have shown that with co-administration of bicalutamide, mean midazolam (a CYP 3A4 substrate) levels may be increased 1.5-fold (for Cmax) and 1.9-fold (for AUC). Hence, caution should be exercised when bicalutamide is co-administered with CYP 3A4 substrates.

In vitroprotein binding studies have shown that bicalutamide can displace coumarin anticoagulants from binding sites. PT/INR should be closely monitored in patients concomitantly receiving coumarin anticoagulants and bicalutamide. Adjustment of the anticoagulant dose may be necessary [see Warnings and Precautions (5.2)and Adverse Reactions (6.2)].

8. USE IN SPECIFIC POPULATIONS

8.1. Pregnancy

Risk Summary

Bicalutamide tablets are contraindicated for use in pregnant women because it can cause fetal harm. Bicalutamide tablets are not indicated for use in females. There are no human data on the use of bicalutamide tablets in pregnant women. In animal reproduction studies, oral administration of bicalutamide to pregnant rats during organogenesis caused abnormal development of reproductive organs in male fetuses at exposures approximately 0.7 to 2 times the human exposure at the recommended dose (see Data).

Data

Animal Data

In an embryo-fetal development study in pregnant rats dosed during the period of organogenesis from gestation days 6-15, male fetuses had reduced anogenital distance at doses of 10 mg/kg/day and above (approximately 0.7 to 2 times the human exposure at the recommended dose).

In a pre- and post-natal development study, female rats were dosed from gestation day 7-16 and allowed to litter and rear their offspring to weaning. Male offspring of rats receiving doses of 10 mg/kg/day (approximately 0.7 times the human exposure at the recommended dose) and above, were observed to have reduced anogenital distance.

In a peri- and post-natal development study, female rats were dosed from gestation day 16 to lactation day 22 and allowed to litter and rear their offspring to weaning. Survival and weights of offspring during lactation were reduced for litters from maternal rats receiving doses of 250 mg/kg/day (approximately 2 times the human exposure at the recommended dose). Male offspring of rats receiving doses of 10 mg/kg/day (approximately 0.7 times the human exposure at the recommended dose) and above, were observed to have reduced anogenital distance, smaller secondary sex organs, cryptorchidism and hypospadias resulting in an inability to mate and impregnate their female partners. Female offspring of rats receiving doses of 10 mg/kg/day (approximately 0.7 times the human exposure at the recommended dose) and above had reduced pregnancy rates.

8.2. Lactation

Risk Summary

Bicalutamide tablets are is not indicated for use in pregnant women. There is no information available on the presence of bicalutamide in human milk, or on the effects on the breastfed infant or on milk production. Bicalutamide has been detected in rat milk.

8.3. Females and Males of Reproductive Potential

Contraception

Males

Antiandrogen therapy may cause morphological changes in spermatozoa [see Nonclinical Toxicology (13.1)] . Based on findings in animal reproduction studies and its mechanism of action, advise male patients with female partners of reproductive potential to use effective contraception during treatment and for 130 days after the final dose of bicalutamide tablets [see Use in Specific Populations (8.1)and Clinical Pharmacology (12.1)] .

Infertility

Males

Based on animal studies, bicalutamide can lead to inhibition of spermatogenesis and may impair fertility in males of reproductive potential. The long-term effects of bicalutamide on male fertility have not been studied [see Nonclinical Toxicology (13.1)] .

8.4. Pediatric Use

The safety and effectiveness of bicalutamide tablets in pediatric patients have not been established.

Bicalutamide orodispersible tablet was studied in combination with anastrozole orodispersible tablet in an open-label, non-comparative, multi-center study that assessed the efficacy and safety of this combination regimen over 12 months in the treatment of gonadotropin-independent precocious puberty in boys with familial male-limited precocious puberty, also known as testotoxicosis. Patients were enrolled in the study if they had a baseline age ≥2 years and a diagnosis of testotoxicosis based on clinical features of progressive precocious puberty, symmetrical testicular enlargement, advanced bone age, pubertal levels of serum testosterone, prepubertal pattern of gonadotropin secretion following a GnRH stimulation test, and absence of other clinical and biochemical causes of testosterone excess. Thirteen out of the 14 patients enrolled completed 12 months of combination treatment (one patient was lost to follow-up). If central precocious puberty (CPP) developed an LHRH analog was to be added. Four patients were diagnosed with CPP during the 12-month study and received LHRH analog treatment and 2 additional patients were diagnosed at the end of the 12 months and received treatment subsequently. Mean ± SD characteristics at baseline were as follows: chronological age: 3.9±1.9 years; bone age 8.8±2.5; bone age/chronological age ratio: 2.06±0.51; growth rate (cm/yr): 10.81±4.22; growth rate standard deviation score (SDS): 0.41±1.36.

The starting bicalutamide dose was 12.5 mg. Bicalutamide was titrated in each patient until steady-state R-bicalutamide (the active isomer of bicalutamide) trough plasma concentration reached 5-15 mcg/mL, which is the range of therapeutic concentrations achieved in adults with prostate cancer following the administration of the currently approved bicalutamide dose of 50 mg. The starting daily dose of anastrozole was 0.5 mg. Anastrozole was independently titrated in each patient until it reached at steady-state a serum estradiol concentration of <10 pmol/L (2.7 pg/mL). The following ascending doses were used for bicalutamide: 12.5 mg, 25 mg, 50 mg, and 100 mg. For anastrozole there were two ascending doses: 0.5 mg and 1 mg. At the end of the titration phase, 1 patient was on 12.5 mg bicalutamide, 8 patients were on 50 mg bicalutamide, and 4 patients were on 100 mg bicalutamide; 10 patients were on 0.5 mg anastrozole and 3 patients were on 1 mg anastrozole. In the majority of patients, steady-state trough concentrations of R-bicalutamide appeared to be attained by Day 21 with once daily dosing. Steady-state trough plasma anastrozole concentrations appeared to be attained by Day 8.

The primary efficacy analysis of the study was to assess the change in growth rate after 12 months of treatment, relative to the growth rate during the ≥6 months prior to entering the study. Pre-study growth rates were obtained retrospectively. There was no statistical evidence that the growth rate was reduced during treatment. During bicalutamide/anastrozole treatment the mean growth rate (cm/yr) decreased by 1.6 cm/year, 95% CI (-4.7 to 1.5) p=0.28; the mean growth rate SDS decreased by 0.1 SD, 95% CI (-1.2 to 1.0) p=0.88. Table 2 shows descriptive data for growth rates for the overall population and for subgroups defined by history of previous treatment for testotoxicosis with ketoconazole, spironolactone, anastrozole or other aromatase inhibitors.

Table 2. Growth Rates

 | Analysis population | Pre-study Mean | Change from pre-study to 12 months |  |  | % patients with growth reduction^1
 | Analysis population | Pre-study Mean | Mean | Median | (Min, Max) | % patients with growth reduction^1
Growth rate (cm/yr) | All treated (n=13) | 10.8 | -1.6 | -2.8 | (-7.4, 8.4) | 9/13 (69%)
Growth rate (cm/yr) | PT^2(n=6) | 10.3 | -0.2 | -2.6^3 | (-7.2, 8.4) | 4/6 (67%)
Growth rate (cm/yr) | NPT^4(n=7) | 11.2 | -2.8 | -2.8 | (-7.4, 1.1) | 5/7 (71%)
Growth rate (SD units) | All treated (n=13) | 0.4 | -0.1 | -0.4 | (-2.7, 3.5) | 9/13 (69%)
Growth rate (SD units) | PT^2(n=6) | -0.1 | +0.7 | -0.2^3 | (-1.6, 3.5) | 4/6 (67%)
Growth rate (SD units) | NPT^4(n=7) | 0.8 | -0.7 | -0.4 | (-2.7, 0.5) | 5/7 (71%)

1. Change compared to pre study growth rate.
2. PT = Previous treatment for testotoxicosis with ketoconazole, spironolactone, anastrozole or other aromatase inhibitors.
3. Median calculated as midpoint of 3rdand 4thranked observations.
4. NPT = no previous treatment for testotoxicosis with ketoconazole, spironolactone, anastrozole, or other aromatase inhibitors.

Total testosterone concentrations increased by a mean of 5 mmol/L over the 12 months of treatment from a baseline mean of 10 mmol/L. Estradiol concentrations were at or below the level of quantification (9.81 pmol/L) for 11 of 12 patients after 12 months of treatment. Six of the 12 patients started treatment at an estradiol concentration below the level of quantification.

There were no deaths, serious adverse events, or discontinuations due to adverse events during the study. Of the 14 patients exposed to study treatment, 13 (92.9%) experienced at least one adverse event. The most frequently reported (>3 patients) adverse events were gynecomastia (7/14, 50%), central precocious puberty (6/14, 43%), vomiting (5/14, 36%), headache (3/14, 21%), pyrexia (3/14, 21%), and upper respiratory tract infection (3/14, 21%). Adverse reactions considered possibly related to bicalutamide by investigators included gynecomastia (6/14, 43%), central precocious puberty (2/14, 14%), breast tenderness (2/14, 14%), breast pain (1/14, 7%), asthenia (1/14, 7%), increased alanine aminotransferase [ALT] (1/14, 7%), increased aspartate aminotransferase [AST] (1/14, 7%), and musculoskeletal chest pain (1/14, 7%). Headache was the only adverse reaction considered possibly related to anastrozole by investigators. For the patient who developed elevated ALT and AST, the elevation was <3X ULN, and returned to normal without stopping treatment; there was no concomitant elevation in total bilirubin.

8.5. Geriatric Use

In two studies in patients given 50 or 150 mg daily, no significant relationship between age and steady-state levels of total bicalutamide or the active R-enantiomer has been shown.

8.6. Hepatic Impairment

Bicalutamide tablets should be used with caution in patients with moderate-to-severe hepatic impairment. Bicalutamide is extensively metabolized by the liver. Limited data in subjects with severe hepatic impairment suggest that excretion of bicalutamide may be delayed and could lead to further accumulation. Periodic liver function tests should be considered for hepatic-impaired patients on long-term therapy [see Warnings and Precautions (5.1)].

No clinically significant difference in the pharmacokinetics of either enantiomer of bicalutamide was noted in patients with mild-to-moderate hepatic disease as compared to healthy controls. However, the half-life of the R-enantiomer was increased approximately 76% (5.9 and 10.4 days for normal and impaired patients, respectively) in patients with severe liver disease (n=4).

8.7. Renal Impairment

Renal impairment (as measured by creatinine clearance) had no significant effect on the elimination of total bicalutamide or the active R-enantiomer.

10. OVERDOSAGE

Long-term clinical trials have been conducted with dosages up to 200 mg of bicalutamide daily and these dosages have been well tolerated. A single dose of bicalutamide that results in symptoms of an overdose considered to be life threatening has not been established.

There is no specific antidote; treatment of an overdose should be symptomatic.

In the management of an overdose with bicalutamide, vomiting may be induced if the patient is alert. It should be remembered that, in this patient population, multiple drugs may have been taken. Dialysis is not likely to be helpful since bicalutamide is highly protein bound and is extensively metabolized. General supportive care, including frequent monitoring of vital signs and close observation of the patient, is indicated.

11. DESCRIPTION

Bicalutamide Tablets USP contain 50 mg of bicalutamide USP, a non-steroidal androgen receptor inhibitor with no other known endocrine activity. The chemical name is propanamide, N [4 cyano-3-(trifluoromethyl)phenyl]-3-[(4-fluorophenyl)sulfonyl]-2-hydroxy-2-methyl-,(+-). The structural and empirical formulas are:

Bicalutamide has a molecular weight of 430.37. The pKa is approximately 12. Bicalutamide is a fine white to off-white powder which is practically insoluble in water at 37°C (5 mg per 1000 mL), slightly soluble in chloroform and absolute ethanol, sparingly soluble in methanol, and soluble in acetone and tetrahydrofuran.

Bicalutamide is a racemate with its antiandrogenic activity being almost exclusively exhibited by the R-enantiomer of bicalutamide; the S-enantiomer is essentially inactive.

The inactive ingredients of Bicalutamide Tablets USP are lactose, magnesium stearate, hypromellose, polyethylene glycol, polyvidone, sodium starch glycollate, and titanium dioxide.

12. CLINICAL PHARMACOLOGY

12.1. Mechanism of Action

Bicalutamide is a non-steroidal androgen receptor inhibitor. It competitively inhibits the action of androgens by binding to cytosol androgen receptors in the target tissue. Prostatic carcinoma is known to be androgen sensitive and responds to treatment that counteracts the effect of androgen and/or removes the source of androgen.

When bicalutamide is combined with LHRH analog therapy, the suppression of serum testosterone induced by the LHRH analog is not affected. However, in clinical trials with bicalutamide as a single agent for prostate cancer, rises in serum testosterone and estradiol have been noted.

In a subset of patients who have been treated with bicalutamide and an LHRH agonist, and who discontinue bicalutamide therapy due to progressive advanced prostate cancer, a reduction in Prostate Specific Antigen (PSA) and/or clinical improvement (antiandrogen withdrawal phenomenon) may be observed.

12.3. Pharmacokinetics

Absorption

Bicalutamide is well-absorbed following oral administration, although the absolute bioavailability is unknown. Co-administration of bicalutamide with food has no clinically significant effect on rate or extent of absorption.

Distribution

Bicalutamide is highly protein-bound (96%) [see Drug Interactions (7)] .

Metabolism/Elimination

Bicalutamide undergoes stereospecific metabolism. The S (inactive) isomer is metabolized primarily by glucuronidation. The R (active) isomer also undergoes glucuronidation but is predominantly oxidized to an inactive metabolite followed by glucuronidation. Both the parent and metabolite glucuronides are eliminated in the urine and feces. The S-enantiomer is rapidly cleared relative to the R-enantiomer, with the R-enantiomer accounting for about 99% of total steady-state plasma levels.

Pharmacokinetics of the active enantiomer of bicalutamide in normal males and patients with prostate cancer are presented in Table 3.

Table 3. Pharmacokinetics of Bicalutamide Active Enantiomer
Parameter | Mean | Standard Deviation
Normal Males (n=30)
Apparent Oral Clearance (L/hr) | 0.320 | 0.103
1. Single Dose Peak Concentration (mcg/mL) | 0.768 | 0.178
1. Single Dose Time to Peak Concentration (hours) | 31.3 | 14.6
Half-life (days) | 5.8 | 2.29
Patients with Prostate Cancer (n=40)
Css(mcg/mL) | 8.939 | 3.504

13. NONCLINICAL TOXICOLOGY

13.1. Carcinogenesis, Mutagenesis, Impairment of Fertility

Two-year oral carcinogenicity studies were conducted in both male and female rats and mice at doses of 5, 15 or 75 mg/kg/day of bicalutamide. A variety of tumor target organ effects were identified and were attributed to the antiandrogenicity of bicalutamide, namely, testicular benign interstitial (Leydig) cell tumors in male rats at all dose levels (the steady-state plasma concentration with the 5 mg/kg/day dose is approximately 0.7 times the human exposure a the recommended dose) and uterine adenocarcinoma in female rats at 75 mg/kg/day (approximately 1.5 times the human exposure at the recommended dose). There is no evidence of Leydig cell hyperplasia in patients; uterine tumors are not relevant to the indicated patient population.

A small increase in the incidence of hepatocellular carcinoma in male mice given 75 mg/kg/day of bicalutamide (approximately 4 times human exposure at the recommended dose) and an increased incidence of benign thyroid follicular cell adenomas in rats given 5 mg/kg/day (approximately 0.7 times the human exposure at the recommended dose) and above were recorded. These neoplastic changes were progressions of non-neoplastic changes related to hepatic enzyme induction observed in animal toxicity studies. Enzyme induction has not been observed following bicalutamide administration in man. There were no tumorigenic effects suggestive of genotoxic carcinogenesis.

A comprehensive battery of both in vitroand in vivogenotoxicity tests (yeast gene conversion, Ames, E. coli, CHO/HGPRT, human lymphocyte cytogenetic, mouse micronucleus, and rat bone marrow cytogenetic tests) has demonstrated that bicalutamide does not have genotoxic activity.

In repeat-dose toxicology studies, atrophy of seminiferous tubules of the testes has been observed for all species examined, which is a predicted class effect with antiandrogens. In the 6- and 12-month rat study, testicular atrophy was seen at approximately 2 times the human exposure at the recommended dose. In the 12-month dog study, the incidence of testicular atrophy was seen at approximately 7 times the human exposure at the recommended dose. In male rats administered 250 mg/kg/day (approximately 2 times human exposure at the recommended dose), the precoital interval and time to successful mating were increased in the first pairing, but no effects on fertility following successful mating were seen. These effects were reversed by 7 weeks after the end of an 11 week period of dosing.

Female rats dosed at 1, 10 and 250 mg/kg/day (less than to 2 times the human exposure at the recommended dose) had increased estrous cycle irregularity but there was no effect on fertility.

In a peri- and post-natal development study, female offspring of rats receiving doses of 10 mg/kg/day (approximately 0.7 times the human exposure at the recommended clinical dose) and above had reduced pregnancy rates. Administration of bicalutamide to pregnant females resulted in feminization of the male offspring leading to hypospadias at doses of 10 mg/kg/day (approximately 0.7 times the human exposure at the recommended dose) and above. Affected male offspring were also impotent.

14. CLINICAL STUDIES

14.1. Bicalutamide 50 mg Daily in Combination with an LHRH-A

In a multi-center, double-blind, controlled clinical trial, 813 patients with previously untreated advanced prostate cancer were randomized to receive bicalutamide 50 mg once daily (404 patients) or flutamide 250 mg (409 patients) three times a day, each in combination with LHRH analogs (either goserelin acetate implant or leuprolide acetate depot).

In an analysis conducted after a median follow-up of 160 weeks was reached, 213 (52.7%) patients treated with bicalutamide-LHRH analog therapy and 235 (57.5%) patients treated with flutamide-LHRH analog therapy had died. There was no significant difference in survival between treatment groups (see Figure 1). The hazard ratio for time to death (survival) was 0.87 (95% confidence interval 0.72 to 1.05).

Figure 1 - The Kaplan-Meier probability of death for both antiandrogen treatment groups.

There was no significant difference in time to objective tumor progression between treatment groups (see Figure 2). Objective tumor progression was defined as the appearance of any bone metastases or the worsening of any existing bone metastases on bone scan attributable to metastatic disease, or an increase by 25% or more of any existing measurable extraskeletal metastases. The hazard ratio for time to progression of bicalutamide plus LHRH analog to that of flutamide plus LHRH analog was 0.93 (95% confidence interval, 0.79 to 1.10).

Figure 2 - Kaplan-Meier curve for time to progression for both antiandrogen treatment groups.

Quality of life was assessed with self-administered patient questionnaires on pain, social functioning, emotional well-being, vitality, activity limitation, bed disability, overall health, physical capacity, general symptoms, and treatment related symptoms. Assessment of the Quality of Life questionnaires did not indicate consistent significant differences between the two treatment groups.

14.2. Safety Data from Clinical Studies using Bicalutamide 150 mg

Bicalutamide 150 mg is not approved for use either alone or with other treatments.

Two identical multi-center, randomized, open-label trials comparing bicalutamide 150 mg daily monotherapy to castration were conducted in patients that had locally advanced (T3-4, NX, M0) or metastatic (M1) prostate cancer.

Monotherapy – M1 Group

Bicalutamide 150 mg daily is not approved for use in patients with M1 cancer of the prostate. Based on an interim analysis of the two trials for survival, the Data Safety Monitoring Board recommended that bicalutamide treatment be discontinued in the M1 patients because the risk of death was 25% (HR 1.25, 95% CI 0.87 to 1.81) and 31% (HR 1.31, 95% CI 0.97 to 1.77) higher in the bicalutamide treated group compared to that in the castrated group, respectively.

Locally Advanced (T3-4, NX, M0) Group

Bicalutamide 150 mg daily is not approved for use in patients with locally advanced (T3-4, NX, M0) cancer of the prostate. Following discontinuation of all M1 patients, the trials continued with the T3-4, NX, M0 patients until study completion. In the larger trial (N=352), the risk of death was 25% (HR 1.25, 95% CI 0.92 to 1.71) higher in the bicalutamide group and in the smaller trial (N=140), the risk of death was 36% (HR 0.64, 95% CI, 0.39 to 1.03) lower in the bicalutamide group.

In addition to the above two studies, there are three other ongoing clinical studies that provide additional safety information for bicalutamide 150 mg, a dose that is not approved for use. These are three multi-center, randomized, double-blind, parallel group trials comparing bicalutamide 150 mg daily monotherapy (adjuvant to previous therapy or under watchful waiting) with placebo, for death or time to disease progression, in a population of 8113 patients with localized or locally advanced prostate cancer.

Bicalutamide 150 mg daily is not approved for use as therapy for patients with localized prostate cancer who are candidates for watchful waiting. Data from a planned subgroup analysis of two of these trials in 1627 patients with localized prostate cancer who were under watchful waiting, revealed a trend toward decreased survival in the bicalutamide arm after a median follow-up of 7.4 years. There were 294 (37.7%) deaths in the bicalutamide treated patients versus 279 (32.9%) deaths in the placebo-treated patients (localized watchful waiting group) for a hazard ratio of 1.16 (95% CI 0.99 to 1.37).

16. HOW SUPPLIED/STORAGE AND HANDLING

White, film-coated tablets (identified on one side with "Cdx50" and on the reverse with the CASODEX logo) are supplied in unit dose bottles of 30 tablets (51407-010-30).

16.1. Storage and Handling

Store at controlled room temperature, 20° to 25°C (68° to 77°F) [see USP].

17. PATIENT COUNSELING INFORMATION

Advise the patient to read the FDA-approved patient labeling (Patient Information).

Dose and Schedule:Inform patients that therapy with bicalutamide tablets and the LHRH analog should be started at the same time and that they should not interrupt or stop taking these medications without consulting their healthcare provider [see Dosage and Administration (2.1)] .

Hepatitis:Inform patients that bicalutamide tablets can cause hepatitis, which may result in hepatic failure and death. Advise patients that liver function tests should be monitored regularly during treatment and to report signs and symptoms of hepatitis [see Warnings and Precautions (5.1)] .

Hemorrhage with Concomitant Use of Coumarin Anticoagulant:Inform patients that serious bleeding has occurred with reported increased anticoagulant effects while taking bicalutamide tablets. Advise patients to notify their healthcare provider of any bleeding or spontaneous bruising while on bicalutamide tablets and taking anticoagulants [see Warnings and Precautions (5.2)and Adverse Reactions (6.2)] .

Glucose Tolerance:Inform patients that diabetes or loss of glycemic control in patients with pre-existing diabetes has been reported during treatment with LHRH agonists. Consideration should therefore be given to monitoring blood glucose in patients receiving bicalutamide tablets in combination with LHRH agonists [see Warnings and Precautions (5.4)].

Somnolence:During treatment with bicalutamide tablets, somnolence has been reported. Advise patients who experience this symptom to observe caution when driving or operating machines [see Adverse Reactions (6.1)] .

Photosensitivity:Inform patients that cases of photosensitivity have been reported during treatment with bicalutamide tablets and that they should avoid direct exposure to excessive sunlight or UV-light exposure. Consideration should be given to the use of sunscreen [see Adverse Reactions (6.2)] .

Contraception and Fertility:Advise male patients with female partners of reproductive potential to use effective contraception during treatment and for 130 days after the last dose of bicalutamide tablets therapy. Advise male patients that bicalutamide tablets may impair fertility [see Use in Specific Populations (8.3)].

Manufactured by:
Corden Pharma GmbH, Otto-Hahn-Strasse
68723 Plankstadt, Germany

Distributed by:
ANI Pharmaceuticals, Inc.
Baudette, MN 56623

Marketed by:

GSMS, Inc.

Camarillo, CA 93012 USA

PATIENT INFORMATION

Bicalutamide (BYE-ka-LOO-ta-mide) Tablets

What are bicalutamide tablets?

Bicalutamide tablets are a prescription medicine called an androgen receptor inhibitor, used in combination with luteinizing hormone-releasing hormone (LHRH) medicines to treat Stage D2metastatic prostate cancer.

Bicalutamide tablets 150 mg daily is not approved for use alone or with other treatments.

It is not known if bicalutamide tablets are safe and effective in children.

Do not take bicalutamide tablets if you are:

- allergic to bicalutamide or any of the ingredients in bicalutamide tablets. See the end of this Patient Information leaflet for a complete list of ingredients in bicalutamide tablets. Get medical help right away if you develop any of the following symptoms of an allergic reaction:
  - itching
  - swelling of the face, lips or tongue
  - hives (raised bumps)
  - trouble breathing or swallowing
- female. Bicalutamide tablets are not for use by women.
- pregnant or may become pregnant. Bicalutamide Tablets may harm your unborn baby.

Before taking bicalutamide tablets, tell your healthcare provider about all your medical conditions, including if you:

- have liver problems.
- take a medicine to thin your blood. Ask your healthcare provider or pharmacist if you are not sure if your medicine is a blood thinner.
- have diabetes.
- have a female partner who can become pregnant. Males who have a female partner who can become pregnant should use effective birth control during treatment with bicalutamide tablets and for 130 days after the final dose. Talk to your healthcare provider if you have any questions about birth control.

Tell your healthcare provider about all the medicines you take,including prescription and over-the-counter medicines, vitamins, and herbal supplements. Bicalutamide tablets may affect the way other medicines work and other medicines may affect how bicalutamide tablets work, causing side effects.

Know the medicines you take. Keep a list of your medicines with you to show your healthcare providers when you get a new medicine.

How should I take bicalutamide tablets?

- Take bicalutamide tablets exactly as your healthcare provider tells you to take it.
- Do not stop taking bicalutamide tablets unless your healthcare provider tells you to.
- Bicalutamide tablets can be taken either in the morning or in the evening, but you should take it at the same time every day.
- Your treatment with bicalutamide tablets should start at the same time as your treatment with the LHRH medicine.
- If you miss a bicalutamide tablets dose do not take the missed dose, take the next dose at your next scheduled time. Do not take 2 doses at the same time.
- Bicalutamide tablets can be taken with or without food.
- If you take too much bicalutamide tablets, call your healthcare provider or go to the nearest hospital emergency room right away.

What should I avoid during treatment with bicalutamide tablets?

- Do not drive, operate machinery, or do other dangerous activities until you know how bicalutamide tablets affects you. Bicalutamide tablets can make you sleepy.
- Avoid sunlight, sunlamps, and tanning beds, and consider using sunscreen during treatment with bicalutamide tablets. Some people have had skin sensitivity to sunlight during treatment with bicalutamide tablets.

What are the possible side effects of bicalutamide tablets?

Bicalutamide tablets may cause serious side effects, including:

- Liver problems.Severe liver problems, including liver failure that may need to be treated in a hospital or that may lead to death have happened in people who take bicalutamide tablets. Your healthcare provider should do blood tests to check your liver function before and during treatment with bicalutamide tablets. Tell your healthcare provider right away if you develop any of these symptoms of liver problems during treatment:
  - yellowing of the skin and eyes (jaundice)
  - dark urine
  - right upper stomach pain
  - nausea
  - vomiting
  - tiredness
  - loss of appetite
  - chills
  - fever
- Bleeding problems.Serious bleeding problems have happened in people who take bicalutamide tablets in combination with a blood thinner medicine (coumarin anticoagulants). Bleeding problems have happened days to weeks after starting bicalutamide tablets treatment. If you take a blood thinner medicine during treatment with bicalutamide tablets, tell your healthcare provider if you develop any bleeding or unexplained bruising.
- Breast enlargement (gynecomastia) and breast pain.
- Blood sugar problems.Poor blood sugar control can happen in people who take bicalutamide tablets in combination with LHRH medicines.

Your healthcare provider may do blood tests during treatment with bicalutamide tablets to check for side effects.

Your prostate cancer may get worse during treatment with bicalutamide tablets in combination with LHRH medicines. Regular monitoring of your prostate cancer with your healthcare provider is important to determine if your disease is worse.

Tell your healthcare provider if you have trouble breathing with or without a cough or fever. Some people taking bicalutamide tablets get an inflammation in the lungs called interstitial lung disease.

The most common side effects of bicalutamide tablets include:

- hot flashes (short periods of feeling warm and sweating)
- body pain (including back, pelvis, stomach)
- feeling weak
- constipation
- infection
- nausea
- swelling in your arms, ankles, legs or feet
- shortness of breath (dyspnea)
- dizziness
- diarrhea
- blood in your urine
- frequent urination at night
- a decrease in red blood cells (anemia)

Bicalutamide tablets may have an effect on male fertility which could be reversible. Talk to your healthcare provider if this is a concern for you.

Tell your healthcare provider if you have any side effect that bothers you or that does not go away.

These are not all the possible side effects of bicalutamide tablets. For more information, ask your healthcare provider or pharmacist.

Call your doctor for medical advice about side effects. You may report side effects to FDA at 1-800-FDA-1088.

How should I store bicalutamide tablets?

Store bicalutamide tablets at room temperature between 68°F to 77°F (20°C to 25°C).

Keep bicalutamide tablets and all medicines out of the reach of children.

General information about the safe and effective use of bicalutamide tablets.

Medicines are sometimes prescribed for purposes other than those listed in a Patient Information leaflet. Do not use bicalutamide tablets for a condition for which it was not prescribed. Do not give bicalutamide tablets to other people, even if they have the same symptoms that you have. It may harm them. This Patient Information leaflet summarizes the most important information about bicalutamide tablets. If you would like more information about bicalutamide tablets, talk with your healthcare provider. You can ask your healthcare provider or pharmacist for information about bicalutamide tablets that is written for health professionals.

What are the ingredients in bicalutamide tablets?

Active ingredient: bicalutamide

Inactive ingredients: lactose, magnesium stearate, hypromellose, polyethylene glycol, polyvidone, sodium starch glycollate, titanium dioxide

Manufactured by: Corden Pharma GmbH, Otto-Hahn-Strasse, 68723 Plankstadt, Germany
Distributed by: ANI Pharmaceuticals, Inc., Baudette, MN 56623

For more information, call 1-800-308-6755.

This Patient Information has been approved by the U.S. Food and Drug Administration.

Revised: 6/2020

Marketed by:

GSMS, Inc.

Camarillo, CA 93012 USA

PACKAGE/LABEL PRINCIPAL DISPLAY PANEL

NDC 51407-010-30
Bicalutamide Tablets USP
50 mg
Rx only
30 Tablets